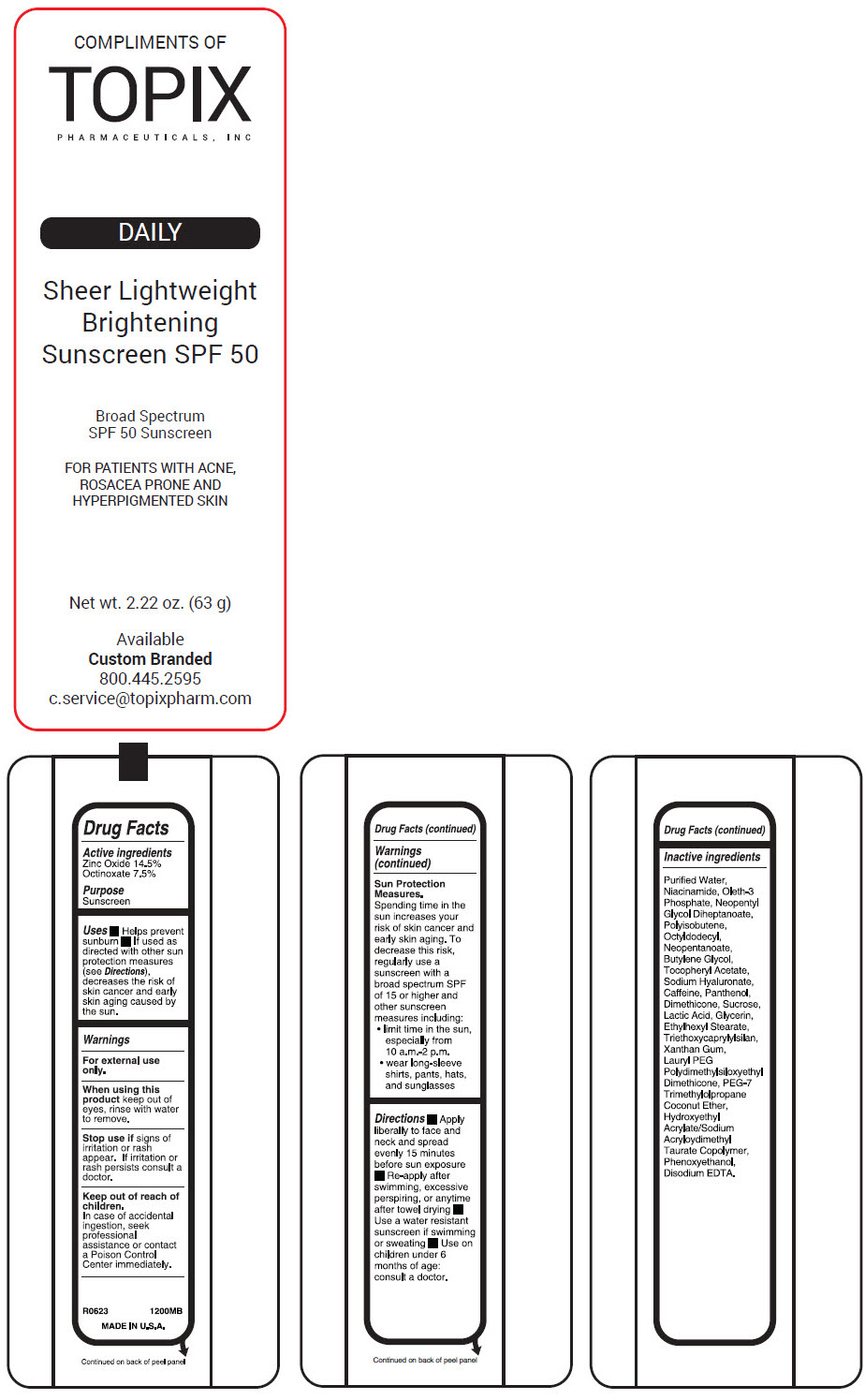 DRUG LABEL: Essential Sheer 
NDC: 51326-200 | Form: LOTION
Manufacturer: Topiderm, Inc.
Category: otc | Type: HUMAN OTC DRUG LABEL
Date: 20240731

ACTIVE INGREDIENTS: ZINC OXIDE 145 mg/1 g; TITANIUM DIOXIDE 75 mg/1 g
INACTIVE INGREDIENTS: WATER; NIACINAMIDE; OLETH-3 PHOSPHATE; NEOPENTYL GLYCOL DIHEPTANOATE; HYDROGENATED POLYISOBUTENE (1300 MW); OCTYLDODECYL NEOPENTANOATE; BUTYLENE GLYCOL; .ALPHA.-TOCOPHEROL ACETATE; HYALURONATE SODIUM; CAFFEINE; PANTHENOL; DIMETHICONE; SUCROSE; LACTIC ACID, UNSPECIFIED FORM; GLYCERIN; ETHYLHEXYL STEARATE; TRIETHOXYCAPRYLYLSILANE; XANTHAN GUM; PEG-7 TRIMETHYLOLPROPANE COCONUT ETHER; PHENOXYETHANOL; EDETATE DISODIUM; HYDROXYETHYL ACRYLATE/SODIUM ACRYLOYLDIMETHYL TAURATE COPOLYMER (100000 MPA.S AT 1.5%)

Essential Sheer
SPF 50

Drug Facts

Active ingredients

Zinc Oxide 14.5%

Octinoxate 7.5%

Purpose

Sunscreen

Uses

- Helps prevent sunburn
- If used as directed with other sun protection measures (see Directions), decreases the risk of skin cancer and early skin aging caused by the sun.

Warnings

For external use only.

When using this product keep out of eyes, rinse with water to remove.

Stop use if signs of irritation or rash appear. If irritation or rash persists consult a doctor.

Keep out of reach of children.

In case of accidental ingestion, seek professional assistance or contact a Poison Control Center immediately.

Sun Protection Measures.

Spending time in the sun increases your risk of skin cancer and early skin aging. To decrease this risk, regularly use a sunscreen with a broad spectrum SPF of 15 or higher and other sunscreen measures including:

- limit time in the sun, especially from 10 a.m.-2 p.m.
- wear long-sleeve shirts, pants, hats, and sunglasses

Directions

- Apply liberally to face and neck and spread evenly 15 minutes before sun exposure
- Re-apply after swimming, excessive perspiring, or anytime after towel drying
- Use a water resistant sunscreen if swimming or sweating
- Use on children under 6 months of age: consult a doctor.

Inactive ingredients

Purified Water, Niacinamide, Oleth-3 Phosphate, Neopentyl Glycol Diheptanoate, Polyisobutene, Octyldodecyl, Neopentanoate, Butylene Glycol, Tocopheryl Acetate, Sodium Hyaluronate, Caffeine, Panthenol, Dimethicone, Sucrose, Lactic Acid, Glycerin, Ethylhexyl Stearate, Triethoxycaprylylsilan, Xanthan Gum, Lauryl PEG Polydimethylsiloxyethyl Dimethicone, PEG-7 Trimethylolpropane Coconut Ether, Hydroxyethyl Acrylate/Sodium Acryloydimethyl Taurate Copolymer, Phenoxyethanol, Disodium EDTA.

PRINCIPAL DISPLAY PANEL - 63 g Bottle Label

COMPLIMENTS OF
TOPIX
PHARMACEUTICALS, INC

DAILY

Sheer Lightweight
Brightening
Sunscreen SPF 50

Broad Spectrum
SPF 50 Sunscreen

FOR PATIENTS WITH ACNE,
ROSACEA PRONE AND
HYPERPIGMENTED SKIN

Net wt. 2.22 oz. (63 g)

Available
Custom Branded
800.445.2595
c.service@topixpharm.com